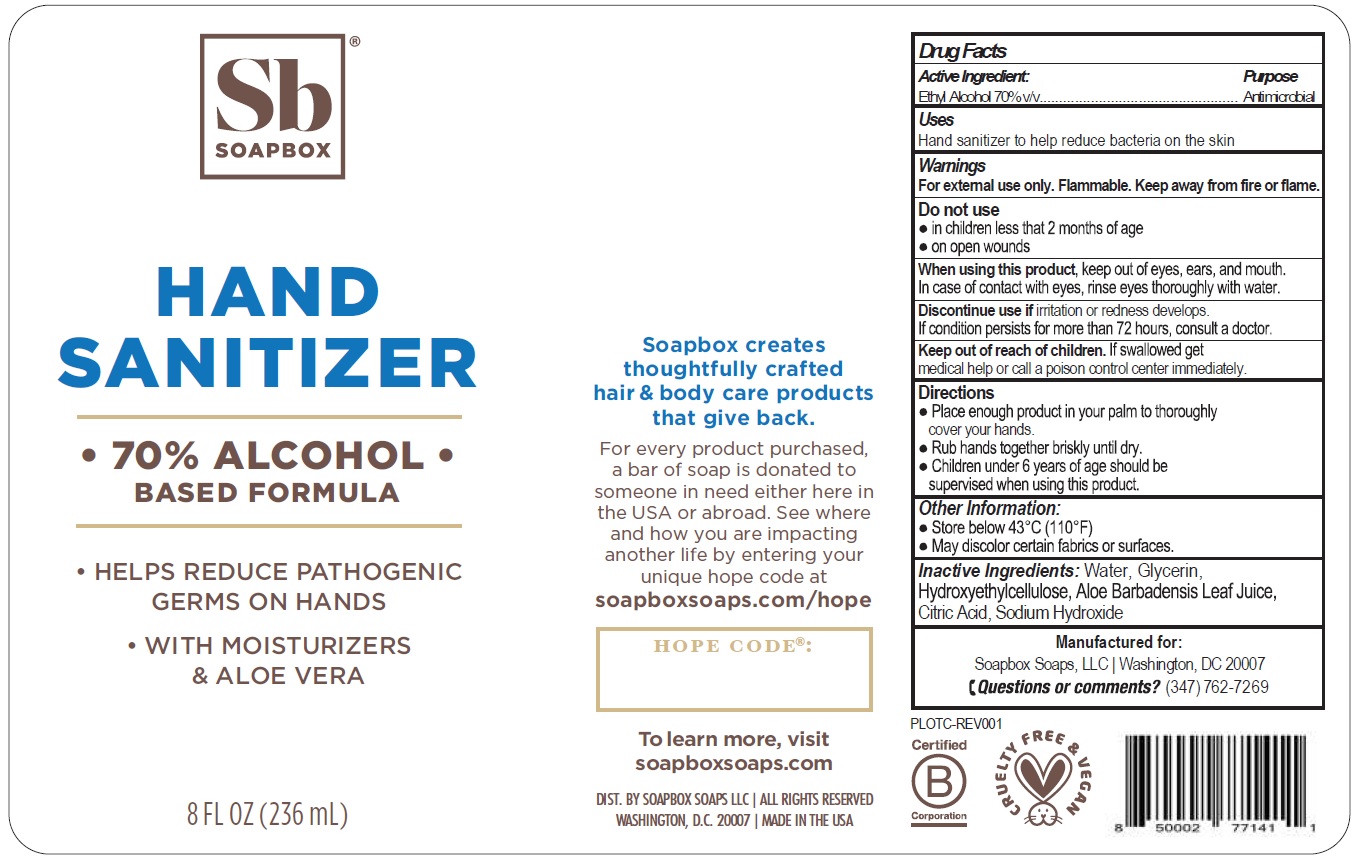 DRUG LABEL: Soapbox Hand Sanitizer
NDC: 75115-002 | Form: GEL
Manufacturer: Soapbox Soaps, LLC
Category: otc | Type: HUMAN OTC DRUG LABEL
Date: 20201230

ACTIVE INGREDIENTS: ALCOHOL 0.7 mL/1 mL
INACTIVE INGREDIENTS: WATER; GLYCERIN; HYDROXYETHYL CELLULOSE, UNSPECIFIED; ALOE VERA LEAF; CITRIC ACID MONOHYDRATE; SODIUM HYDROXIDE

Soapbox Hand Sanitizer

Active Ingredient:

Ethyl Alcohol 70% v/v

Purpose

Antimicrobial

Uses

Hand sanitizer to help reduce bacteria on the skin

Warnings

For external use only. Flammable. Keep away from fire or flame.

Do not use

- in children less than 2 months of age
- on open skin wounds

When using this product,

keep out of eyes, ears, and mouth. In case of contact with eyes, rinse eyes thoroughly with water.

Discontinue use if

irritation or redness develops. If condition persists for more than 72 hours, consult a doctor.

Keep out of reach of children.

If swallowed get medical help or call a poison control center immediately.

Directions

- Place enough product in your palm to thoroughly cover your hands.
- Rub hands together briskly untill dry.
- Children under 6 years of age should be supervised when using this product.

Other Information:

- Store below 43°C (110°F)
- May discolor certain fabrics or surfaces.

Inactive Ingredients:

Water, Glycerin, Hydroxyethylcellulose, Aloe Barbadensis Leaf Juice, Citric Acid, Sodium Hydroxide